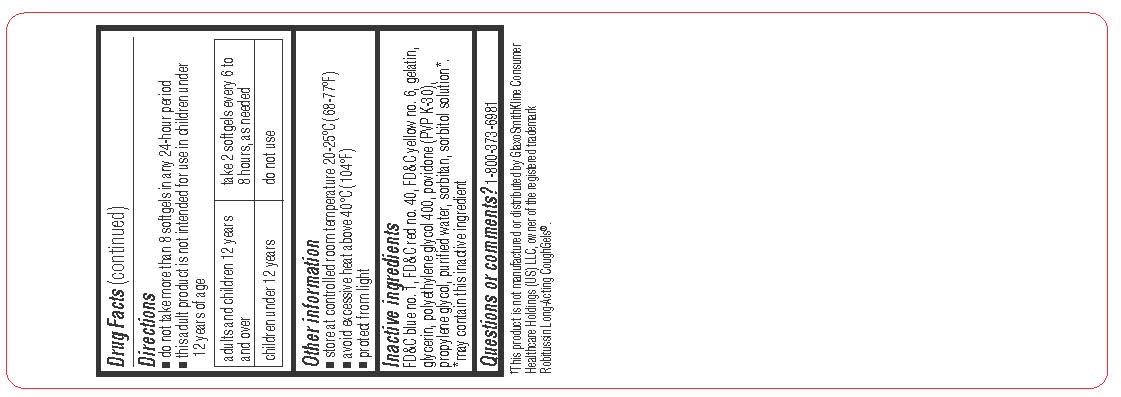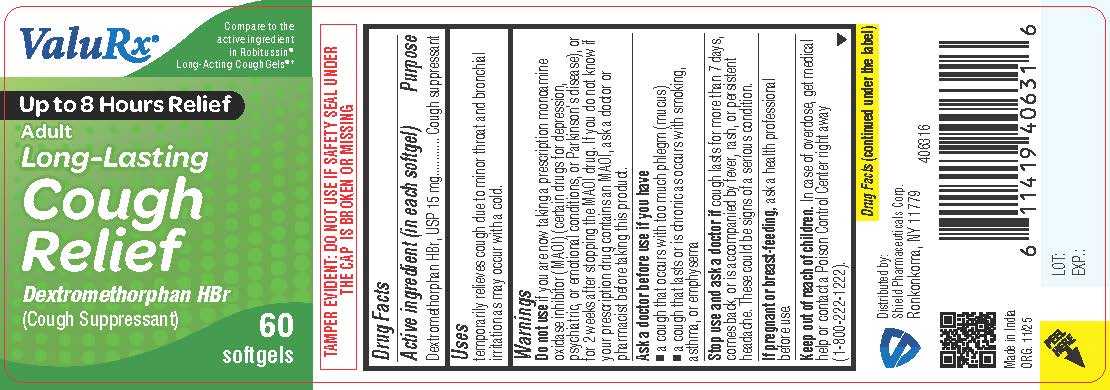 DRUG LABEL: Adult Long Lasting Cough Relief
NDC: 83059-0116 | Form: CAPSULE, LIQUID FILLED
Manufacturer: Shield Pharmaceuticals Corp
Category: otc | Type: HUMAN OTC DRUG LABEL
Date: 20251204

ACTIVE INGREDIENTS: DEXTROMETHORPHAN HYDROBROMIDE 15 mg/1 1
INACTIVE INGREDIENTS: FD&C BLUE NO. 1; FD&C RED NO. 40; FD&C YELLOW NO. 6; GELATIN; GLYCERIN; POLYETHYLENE GLYCOL 400; POVIDONE; PROPYLENE GLYCOL; SORBITAN; SORBITOL SOLUTION; WATER

Adult Long Lasting Cough Relief

Drug Facts

Active ingredient (in each softgel)

Dextromethorphan HBr, USP 15 mg

Purpose

Cough suppressant

Uses

temporarily relieves cough due to minor throat and bronchial irritation as may occur with a cold.

Warnings

Do not use
if you are now taking a prescription monoamine oxidase inhibitor (MAOI) (certain drugs for depression, psychiatric, or emotional conditions, or Parkinson's disease), or for 2 weeks after stopping the MAOI drug. If you do not know if your prescription drug contains an MAOI, ask a doctor or pharmacist before taking this product.

Ask a doctor before use if you have
• a cough that occurs with too much phlegm (mucus)
• a cough that lasts or is chronic as occurs with smoking, asthma, or emphysema

Stop use and ask a doctor ifcough lasts for more than 7 days, comes back, or is accompanied by fever, rash, or persistent headache. These could be signs of a serious condition.

PREGNANCY OR BREAST FEEDING

If pregnant or breast-feeding,ask a health professional before use.

Keep out of reach of children.In case of overdose, get medical help or contact a Poison Control Center right away (1-800-222-1222).

Directions

do not take more than 8 softgels in any 24-hour period
this adult product is not intended for use in children under 12 years of age

adults and children 12 years and over | take 2 softgels every 6 to 8 hours, as needed
children under 12 years | do not use

Other information

• store at controlled room temperature 20-25ºC (68-77ºF)
• avoid excessive heat above 40°C (104°F)
• protect from light

Questions or comments?

1-800-373-6981 (toll-free)

Inactive ingredients

FD&C blue no. 1, FD&C red no. 40, FD&C yellow 6, gelatin, glycerin, polyethylene glycol 400, povidone (pvp k 30), propylene glycol, purified water, sorbitan, sorbitol solution*. *may contain this inactive ingredient

Distributed by:
Shield Pharmaceuticals Corp.
Ronkonkoma, NY 11779

PRINCIPAL DISPLAY PANEL

ValuRx

Compare to the active ingredient in Robitussin® Long-Acting Coughgels®†

Up to 8 Hr. Relief

Adult Long-Lasting
Cough Relief
Dextromethorphan HBr
(Cough Suppressant)